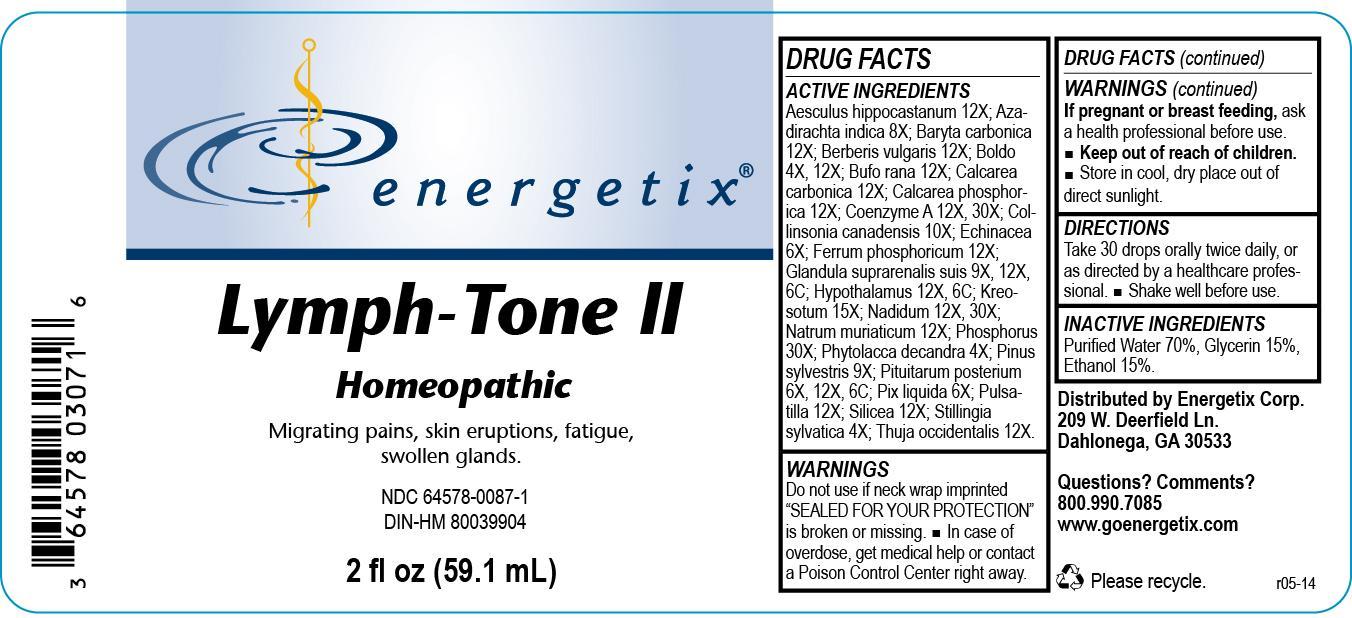 DRUG LABEL: Lymph-Tone II
NDC: 64578-0087 | Form: LIQUID
Manufacturer: Energetix Corp
Category: homeopathic | Type: HUMAN PRESCRIPTION DRUG LABEL
Date: 20140205

ACTIVE INGREDIENTS: HORSE CHESTNUT 12 [hp_X]/59.1 mL; AZADIRACHTA INDICA BARK 8 [hp_X]/59.1 mL; BARIUM CARBONATE 12 [hp_X]/59.1 mL; BERBERIS VULGARIS ROOT BARK 12 [hp_X]/59.1 mL; PEUMUS BOLDUS LEAF 4 [hp_X]/59.1 mL; BUFO BUFO CUTANEOUS GLAND 12 [hp_X]/59.1 mL; OYSTER SHELL CALCIUM CARBONATE, CRUDE 12 [hp_X]/59.1 mL; TRIBASIC CALCIUM PHOSPHATE 12 [hp_X]/59.1 mL; COENZYME A 12 [hp_X]/59.1 mL; COLLINSONIA CANADENSIS ROOT 10 [hp_X]/59.1 mL; ECHINACEA ANGUSTIFOLIA 6 [hp_X]/59.1 mL; FERRUM PHOSPHORICUM 12 [hp_X]/59.1 mL; SUS SCROFA ADRENAL GLAND 9 [hp_X]/59.1 mL; BOS TAURUS HYPOTHALAMUS 12 [hp_X]/59.1 mL; WOOD CREOSOTE 15 [hp_X]/59.1 mL; NADIDE 12 [hp_X]/59.1 mL; SODIUM CHLORIDE 12 [hp_X]/59.1 mL; PHOSPHORUS 30 [hp_X]/59.1 mL; PHYTOLACCA AMERICANA ROOT 4 [hp_X]/59.1 mL; PINUS SYLVESTRIS LEAFY TWIG 9 [hp_X]/59.1 mL; SUS SCROFA PITUITARY GLAND 6 [hp_X]/59.1 mL; PINE TAR 6 [hp_X]/59.1 mL; PULSATILLA VULGARIS 12 [hp_X]/59.1 mL; SILICON DIOXIDE 12 [hp_X]/59.1 mL; STILLINGIA SYLVATICA ROOT 4 [hp_X]/59.1 mL; THUJA OCCIDENTALIS LEAFY TWIG 12 [hp_X]/59.1 mL
INACTIVE INGREDIENTS: WATER 41.361483 mL/59.1 mL; ALCOHOL 8.863175 mL/59.1 mL; GLYCERIN 8.863175 mL/59.1 mL

Lymph-Tone II

ACTIVE INGREDIENT

Aesculus hippocastanum 12X; Azadirachta indica 8X; Baryta carbonica 12X; Berberis vulgaris 12X; Boldo 4X, 12X; Bufo rana 12X; Calcarea carbonica 12X; Calcarea phosphorica 12X; Coenzyme A 12X, 30X; Collinsonia canadensis 10X; Echinacea 6X; Ferrum phosphoricum 12X; Glandula suprarenalis suis 9X, 12X, 6C; Hypothalamus 12X, 6C; Kreosotum 15X; Nadidum 12X, 30X; Natrum muriaticum 12X; Phosphorus 30X; Phytolacca decandra 4X; Pinus sylvestris 9X; Pituitarum posterium 6X, 12X, 6C; Pix liquida 6X; Pulsatilla 12X; Silicea 12X; Stillingia sylvatica 4X; Thuja occidentalis 12X

Do not use if neck wrap imprinted "SEALED FOR YOUR PROTECTION" is broken or missing.

OVERDOSAGE

In case of overdose, get medical help or contact a Poison Control Center right away.

PREGNANCY OR BREAST FEEDING

If pregnant or breast feeding, ask a health professional before use.

Keep out of reach of children.

STORAGE AND HANDLING

Store in cool, dry place out of direct sunlight.

Questions? Comments?

800.990.7085 www.goenergetix.com

PURPOSE

Migrating pains, skin eruptions, fatigue, swollen glands.

INACTIVE INGREDIENT

Purified Water 70%, Glycerin 15%, Ethanol 15%.

DOSAGE AND ADMINISTRATION

Take 30 drops orally twice daily or as directed by a healthcare professional. Shake well before use.

INDICATIONS AND USAGE

Migrating pains, skin eruptions, fatigue, swollen glands.